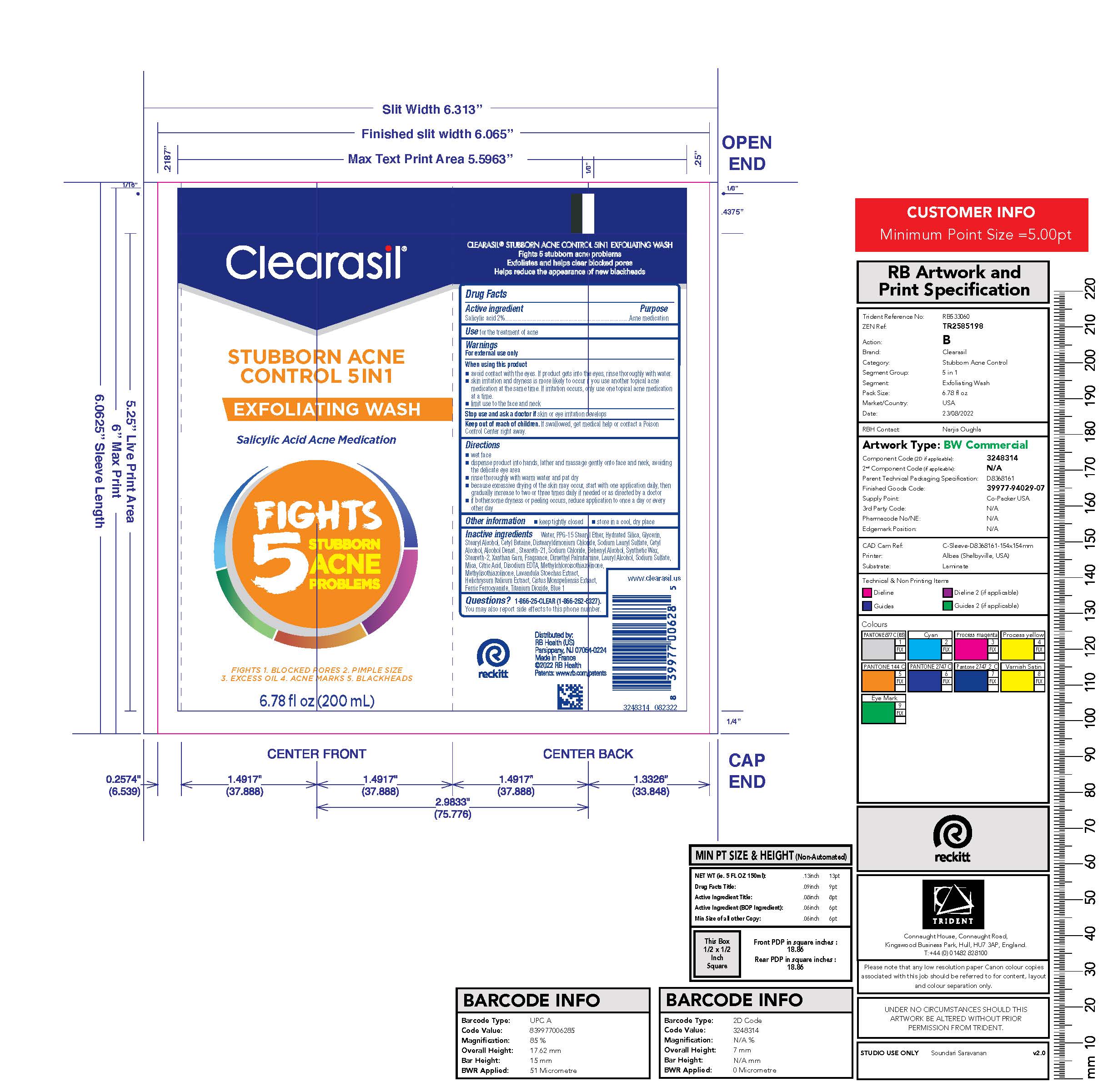 DRUG LABEL: Clearasil Stubborn Acne Control 5in1 Exfoliating Wash
NDC: 63824-436 | Form: LOTION
Manufacturer: RB Health (US) LLC
Category: otc | Type: HUMAN OTC DRUG LABEL
Date: 20241218

ACTIVE INGREDIENTS: SALICYLIC ACID 2 g/100 mL
INACTIVE INGREDIENTS: WATER; PPG-15 STEARYL ETHER; HYDRATED SILICA; GLYCERIN; STEARYL ALCOHOL; CETYL BETAINE; DISTEARYLDIMONIUM CHLORIDE; SODIUM LAURYL SULFATE; CETYL ALCOHOL; ALCOHOL; STEARETH-21; SODIUM CHLORIDE; DOCOSANOL; STEARETH-2; XANTHAN GUM; EDETATE DISODIUM ANHYDROUS; ISOPROPYL ALCOHOL; BUTYLATED HYDROXYTOLUENE; METHYLCHLOROISOTHIAZOLINONE; HELICHRYSUM ITALICUM FLOWER; METHYLISOTHIAZOLINONE; MICA; FERRIC FERROCYANIDE; TITANIUM DIOXIDE; FD&C BLUE NO. 1

Clearasil®Stubborn Acne Control 5in1 Exfoliating Wash

Drug Facts

Active ingredient

Salicylic acid 2%

Purpose

Acne medication

Use

for the treatment of acne

Warnings

For external use only

When using this product

- avoid contact with the eyes. If product gets into the eyes, rinse thoroughly with water.
- skin irritation and dryness is more likely to occur if you use another topical acne medication at the same time. If irritation occurs, only use one topical acne medication at a time.
- limit use to the face and neck

Stop use and ask a doctorif skin or eye irritation develops

Keep out of reach of children.If swallowed, get medical help or contact a Poison Control Center right away.

Directions

- wet face
- dispense product into hands, lather and massage gently onto face and neck, avoiding the delicate eye area
- rinse thoroughly with warm water one too three times daily
- because excessive drying of the skin may occur, start with one application daily, then gradually increase to two or three times daily if needed or as directed by a doctor
- if bothersome dryness or peeling occurs, reduce application to once a day or every other day

Other information

- keep tightly closed
- store in a cool, dry place

Inactive ingredients

Water, PPG-15 Stearyl Ether, Hydrated Silica, Glycerin, Stearyl Alcohol, Cetyl Betaine, Distearyldimonium Chloride, Sodium Lauryl Sulfate, Cetyl Alcohol, Alcohol Denat., Steareth-21, Sodium Chloride, Behenyl Alcohol, Synthetic Wax, Steareth-2, Xanthan Gum, Fragrance, Dimethyl Palmitamine, Lauryl Alcohol, Sodium Sulfate, Mica, Citric Acid, Disodium EDTA, Methylchloroisothiazolinone, Methylisothiazolinone, Lavandula Stoechas Extract, Helicrysum Italicum Extract, Cistus Monspeliensis Extract, Ferric Ferrocyanide, Titanium Dioxide, Blue 1

Questions?

1-866-25-CLEAR (1-866-252-5327).
You may also report side effects to this phone number.

Distributed By:
RB Health (US),
Parsippany, NJ 07054-0224

Made in France

PRINCIPAL DISPLAY PANEL - 200 mL Tube Label

Clearasil®

STUBBORN ACNE
CONTROL 5IN1

EXFOLIATING WASH

Salicylic Acid Acne Medication

FIGHTS
5
STUBBORN
ACNE
PROBLEMS

FIGHTS 1. BLOCKED PORES 2. PIMPLE SIZE
3. EXCESS OIL 4. ACNE MARKS 5. BLACKHEADS

6.78 fl oz (200 mL)